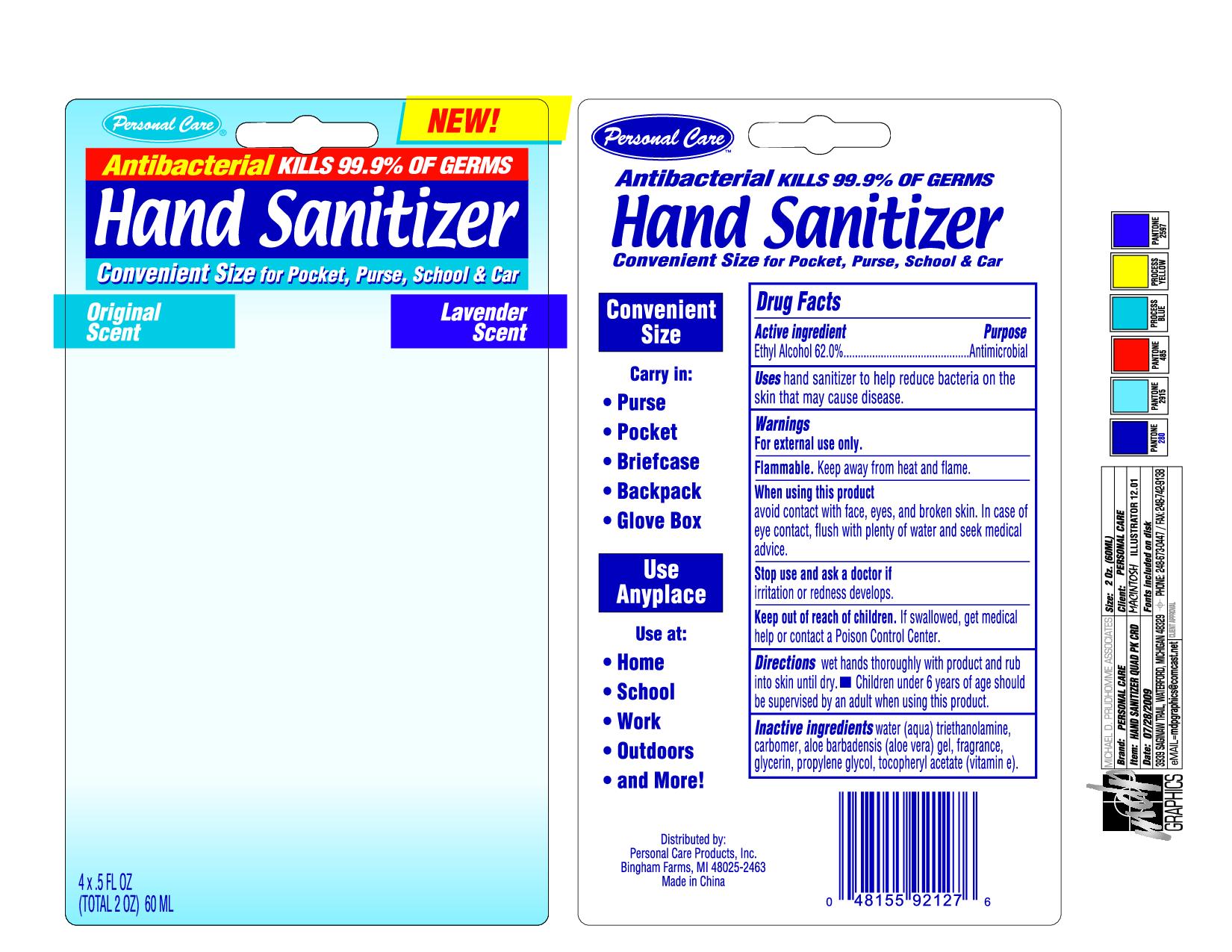 DRUG LABEL: Hand Sanitizer
NDC: 29500-9085 | Form: GEL
Manufacturer: Personal Care Products
Category: otc | Type: HUMAN OTC DRUG LABEL
Date: 20120120

ACTIVE INGREDIENTS: ALCOHOL 9.3 mL/60 mL
INACTIVE INGREDIENTS: WATER; TROLAMINE; ALOE VERA LEAF; GLYCERIN; PROPYLENE GLYCOL; ALPHA-TOCOPHEROL

Personal Care Hand Sanitizer

Active Ingredient

Ethyl Alcohol 62%

Purpose

Antimicrobial

Keep out of reach of children. If swallowed get medical help or contact a Poison Control Center.

INDICATIONS AND USAGE

Uses hand sanitizer to help reduce bacteria on the skin that may cause disease.

Warnings

For external use only.

Flammable. Keep away from heat and flame

When using this product

avoid contact with face, eyes and broken skin. In case of eye contact, flush with plenty of water and seek medical advice.

Stop use and ask a doctor if

irritation or redness develops.

Directions

wet hands thoroughly with product and rub into skin until dry. Children under 6 years of age should be supervised by an adult when using this product.

Inactive Ingredients

water (aqua), triethanolamine, carbomer, aloe barbadensis (aloe vera) gel, fragrance, glycerin, propylene glycol, tocopheryl acetate (vitamin e).